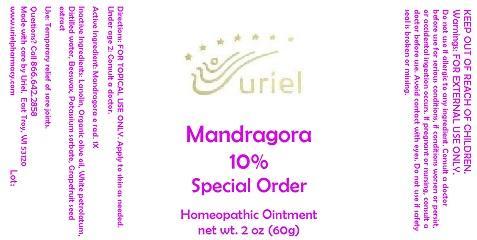 DRUG LABEL: Mandragora 10 Special Order
NDC: 48951-7140 | Form: OINTMENT
Manufacturer: Uriel Pharmacy Inc.
Category: homeopathic | Type: HUMAN OTC DRUG LABEL
Date: 20141216

ACTIVE INGREDIENTS: MANDRAGORA OFFICINARUM ROOT 1 [hp_X]/1 g
INACTIVE INGREDIENTS: LANOLIN; OLIVE OIL; PETROLATUM; WATER; YELLOW WAX; POTASSIUM SORBATE; CITRUS PARADISI SEED

Mandragora 10 Special Order

INDICATIONS AND USAGE

Directions: FOR TOPICAL USE ONLY.

DOSAGE AND ADMINISTRATION

Apply to skin as needed. Under age 2: Consult a doctor.

Active Ingredient: Mandragora e rad. 1X

INACTIVE INGREDIENT

Inactive Ingredients: Lanolin, Organic olive oil, White petrolatum, Distilled water, Beeswax, Potassium sorbate, Grapefruit seed extract

PURPOSE

Use: Temporary relief of sore joints.

KEEP OUT OF REACH OF CHILDREN.

WARNINGS

Warnings: FOR EXTERNAL USE ONLY. Do not use if allergic to any ingredient. Consult a doctor before use for serious conditions, if conditions worsen or persist, or accidental ingestion occurs. If pregnant or nursing, consult a doctor before use. Avoid contact with eyes. Do not use if safety seal is broken or missing.

QUESTIONS

Questions? Call 866.642.2858 Made with care by Uriel, East Troy, WI 53120 www.urielpharmacy.com